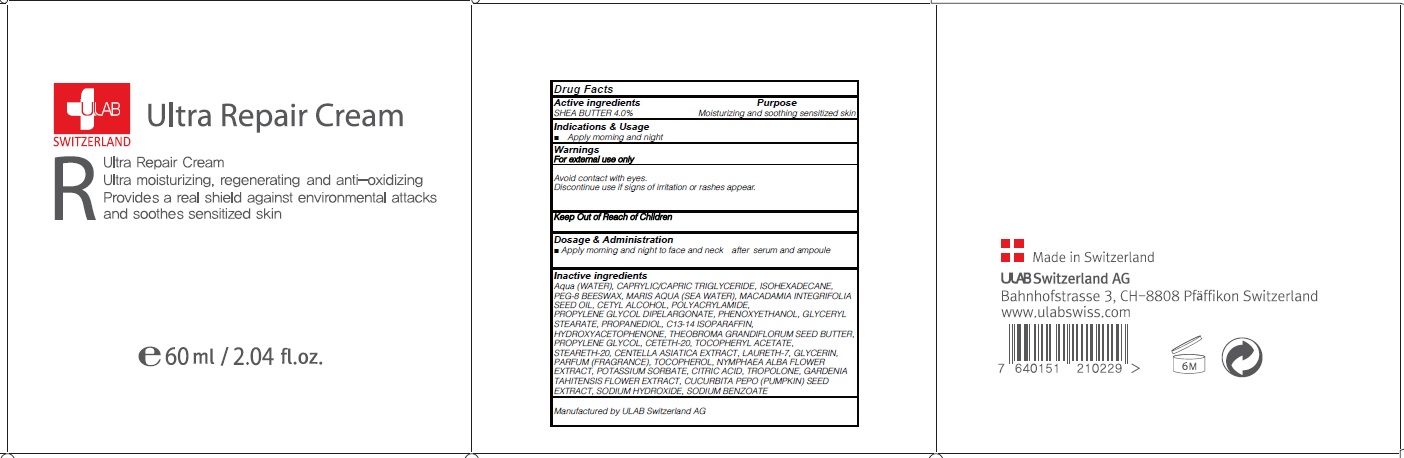 DRUG LABEL: ULTRA REPAIR
NDC: 71276-090 | Form: CREAM
Manufacturer: ULAB
Category: otc | Type: HUMAN OTC DRUG LABEL
Date: 20170322

ACTIVE INGREDIENTS: SHEA BUTTER 2.4 g/60 mL
INACTIVE INGREDIENTS: WATER; ISOHEXADECANE

ACTIVE INGREDIENT

Active ingredients: SHEA BUTTER 4.0%

INACTIVE INGREDIENT

Inactive ingredients: Aqua (WATER), CAPRYLIC/CAPRIC TRIGLYCERIDE, ISOHEXADECANE, PEG-8 BEESWAX, MARIS AQUA (SEA WATER), MACADAMIA INTEGRIFOLIA SEED OIL, CETYL ALCOHOL, POLYACRYLAMIDE, PROPYLENE GLYCOL DIPELARGONATE, PHENOXYETHANOL, GLYCERYL STEARATE, PROPANEDIOL, C13-14 ISOPARAFFIN, HYDROXYACETOPHENONE, THEOBROMA GRANDIFLORUM SEED BUTTER, PROPYLENE GLYCOL, CETETH-20, TOCOPHERYL ACETATE, STEARETH-20, CENTELLA ASIATICA EXTRACT, LAURETH-7, GLYCERIN, PARFUM (FRAGRANCE), TOCOPHEROL, NYMPHAEA ALBA FLOWER EXTRACT, POTASSIUM SORBATE, CITRIC ACID, TROPOLONE, GARDENIA TAHITENSIS FLOWER EXTRACT, CUCURBITA PEPO (PUMPKIN) SEED EXTRACT, SODIUM HYDROXIDE, SODIUM BENZOATE

PURPOSE

Purpose: Moisturizing and soothing sensitized skin

KEEP OUT OF REACH OF CHILDREN

INDICATIONS & USAGE

Indications & Usage: Apply morning and night

WARNINGS

Warnings: For external use only Avoid contact with eyes. Discontinue use if signs of irritation or rashes appear.

DOSAGE & ADMINISTRATION

Dosage & Administration: Apply morning and night to face and neck after serum and ampoule